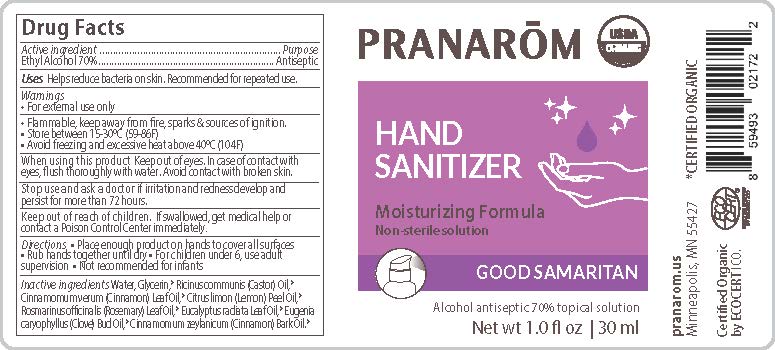 DRUG LABEL: Pranarom Good Samaritan Alcohol antiseptic
NDC: 78596-002 | Form: LIQUID
Manufacturer: Veriditas Botanicals LLC
Category: otc | Type: HUMAN OTC DRUG LABEL
Date: 20200908

ACTIVE INGREDIENTS: ALCOHOL 70 mL/100 mL
INACTIVE INGREDIENTS: CLOVE OIL; EUCALYPTUS RADIATA LEAF OIL; CINNAMON BARK OIL; CINNAMON LEAF OIL; LEMON OIL; ROSEMARY OIL; WATER; GLYCERIN; CASTOR OIL

Hand Sanitizer 2

Active Ingredient(s)

Ethyl Alcohol 70% v/v. Purpose: Antiseptic

Purpose

Antiseptic, Hand Sanitizer

Use

Helps reduce bacteria on skin. Recommended for repeated use.

Warnings

For external use only.

Other information

- Flammable. Keep away from fire, sparks, and sources of ignition.
- Store between 15-30C (59-86F)
- Avoid freezing and excessive heat above 40C (104F)

When using this product Keep out of eyes. In case of contact with eyes, fush thoroughly with water. Avoid contact with broken skin.

Stop use and ask a doctor if irritation and redness develop and persist for more than 72 hours.

Keep out of reach of children. If swallowed, get medical help or contact a Poison Control Center immediately.

Directions

Place enough product on hands to cover all surfaces. Rub hands together until dry. For children under 6, use adult
supervision. Not recommended for infants.

Inactive ingredients

Water, Glycerin,* Ricinus communis (Castor) Oil,* Cinnamomum verum (Cinnamon) Leaf Oil,* Citrus limon (Lemon) Peel Oil,* Rosmarinus officinalis (Rosemary) Leaf Oil,* Eucalyptus radiata Leaf Oil,* Eugenia caryophyllus (Clove) Bud Oil,* Cinnamomum zeylanicum (Cinnamon) Bark Oil.*

Package Label - Principal Display Panel

PRANARÕM

HAND SANITIZER

Moisturizing Formula

Non-Sterile Solution

GOOD SAMARITAN

Alcohol antiseptic 70% topical solution

Net wt xx fl. oz | xx ml

*CERTIFIED ORGANIC

pranarom.us

Minneapolis, MN 55427

Certified Organic

by ECOCERT ICO.